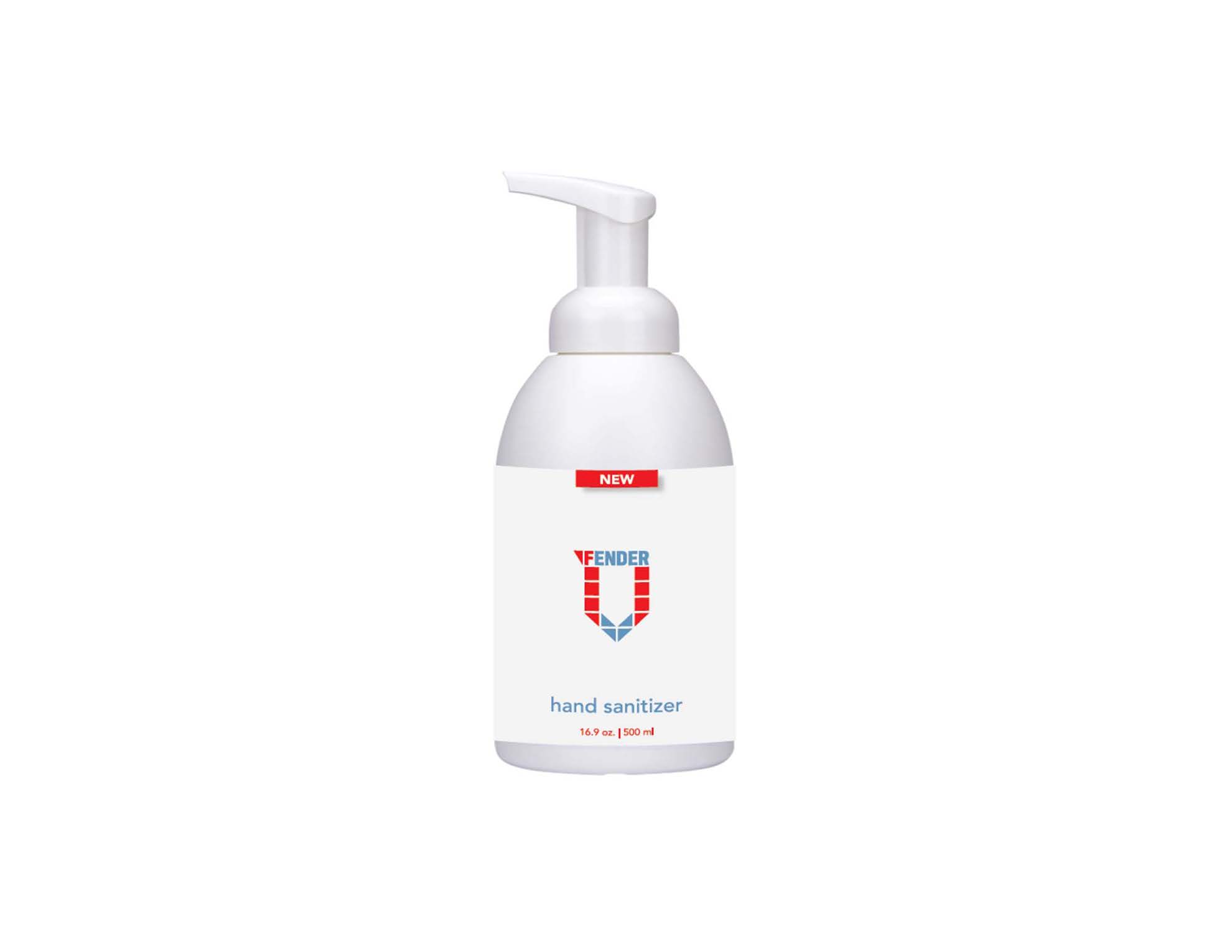 DRUG LABEL: Vfender Hand Sanitizer Gel
NDC: 80387-100 | Form: GEL
Manufacturer: Nara Parts Industries, LLC
Category: otc | Type: HUMAN OTC DRUG LABEL
Date: 20200901

ACTIVE INGREDIENTS: ALCOHOL 72 mL/100 mL
INACTIVE INGREDIENTS: CARBOMER HOMOPOLYMER, UNSPECIFIED TYPE; WATER; GLYCERIN

Active Ingredient(s)

Alcohol 72% v/v. Purpose: Antimicrobial

Purpose

Antimicrobial, Hand Sanitizer

Use

Hand sanitizer to help reduce bacteria on the skin.
Recommended for repeated use.

Warnings

For external use only. Flammable. Keep away from heat or flame

Do not use

- in children less than 2 months of age
- on open skin wounds

When using this product keep out of eyes, ears, and mouth. In case of contact with eyes, rinse eyes thoroughly with water.
Stop use and ask a doctor if irritation or rash occurs. These may be signs of a serious condition.
Keep out of reach of children. If swallowed, get medical help or contact a Poison Control Center right away.

Stop use and ask a doctor if irritation or rash occurs. These may be signs of a serious condition.

Keep out of reach of children. If swallowed, get medical help or contact a Poison Control Center right away.

Directions

- Put enough product in your palm to cover hands and rub hands together briskly until dry.
- Children under 6 years of age should be supervised when using this product.
- Not recommended for infants.

Other information

- Do not store above 105oF (40oC).
- May discolor certain fabrics.
- Harmful to wood finishes and plastics.

Inactive ingredients

Carbomer, Glycerin, Lemon Oil, L-Menthol, Tocopheryl Acetate, Triethanolamine, Water.